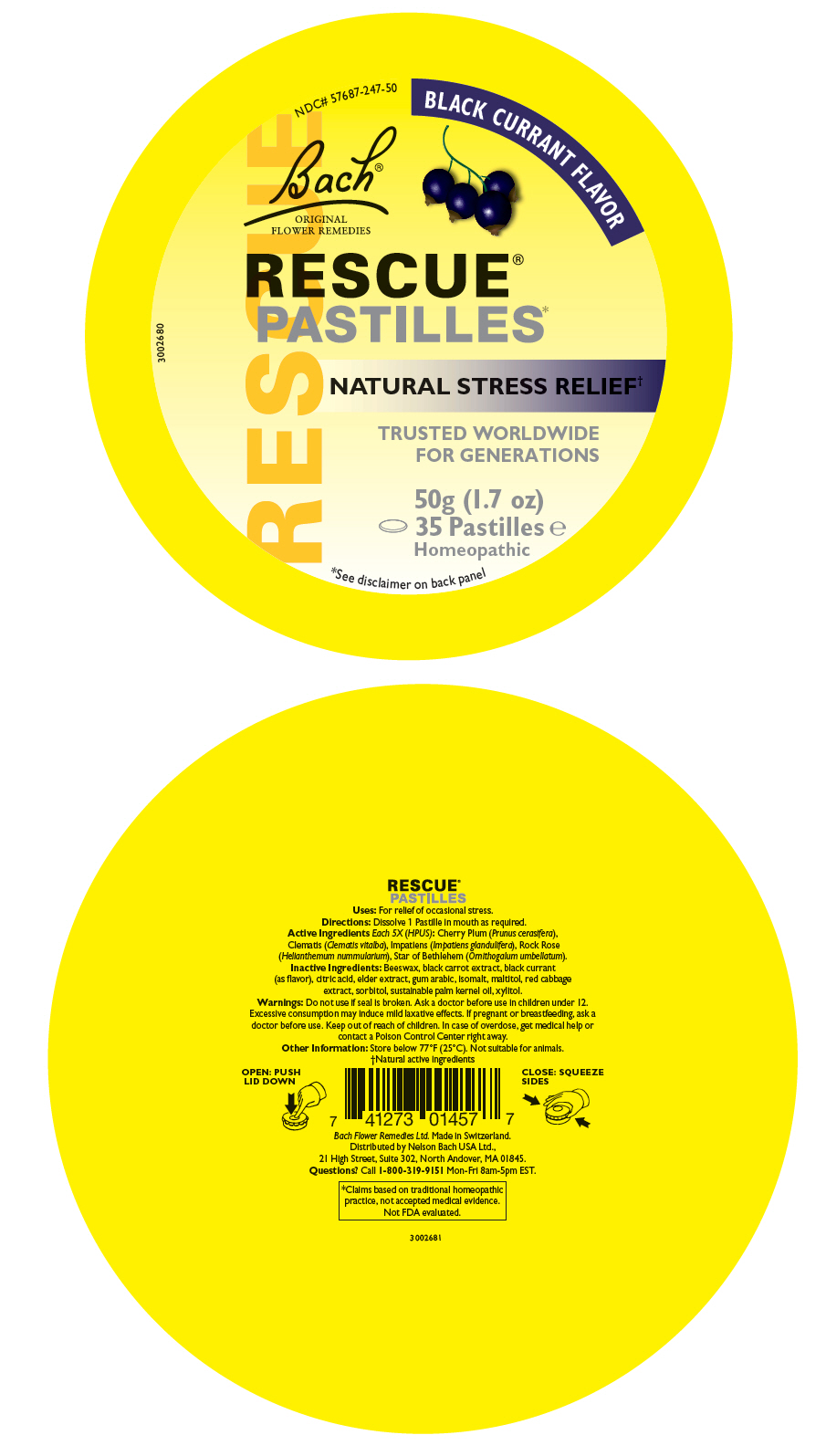 DRUG LABEL: Rescue Pastille Black Currant
NDC: 57687-247 | Form: LOZENGE
Manufacturer: Nelson Bach USA Ltd
Category: homeopathic | Type: HUMAN OTC DRUG LABEL
Date: 20250708

ACTIVE INGREDIENTS: HELIANTHEMUM NUMMULARIUM WHOLE 5 [hp_X]/1 1; CLEMATIS VITALBA WHOLE 5 [hp_X]/1 1; IMPATIENS GLANDULIFERA WHOLE 5 [hp_X]/1 1; PRUNUS CERASIFERA WHOLE 5 [hp_X]/1 1; ORNITHOGALUM UMBELLATUM WHOLE 5 [hp_X]/1 1
INACTIVE INGREDIENTS: SORBITOL; MALTITOL; ISOMALT; ACACIA; CITRIC ACID MONOHYDRATE; XYLITOL; YELLOW WAX; PALM KERNEL OIL

Rescue®Pastille Black Currant

Uses

For relief of occasional stress.

Directions

Dissolve 1 Pastille in mouth as required.

Active Ingredients Each 5X (HPUS)

PURPOSE

Cherry Plum (Prunus cerasifera), Clematis (Clematis vitalba), Impatiens (Impatiens glandulifera), Rock Rose (Helianthemum nummularium), Star of Bethlehem (Ornithogalum umbellatum).

Inactive Ingredients

Beeswax, black carrot extract, black currant (as flavor), citric acid, elder extract, gum arabic, isomalt, maltitol, red cabbage extract, sorbitol, sustainable palm kernel oil, xylitol.

Warnings

Do not use if seal is broken. Ask a doctor before use in children under 12. Excessive consumption may induce mild laxative effects. If pregnant or breastfeeding, ask a doctor before use.

Keep out of reach of children. In case of overdose, get medical help or contact a Poison Control Center right away.

Other Information

Store below 77ºF (25ºC). Not suitable for animals.

Questions?

Call 1-800-319-9151Mon-Fri 8am-5pm EST.

Distributed by Nelson Bach USA Ltd.,
21 High Street, Suite 302, North Andover, MA 01845.

PRINCIPAL DISPLAY PANEL - 50 g Pastille Container Label

RESCUE

NDC# 57687-247-50

BLACK CURRANT FLAVOR

Bach®
ORIGINAL
FLOWER REMEDIES

RESCUE®
PASTILLES*

NATURAL STRESS RELIEF†

TRUSTED WORLDWIDE
FOR GENERATIONS

50g (1.7 oz)
35 Pastilles ℮
Homeopathic

*See disclaimer on back panel

3002680